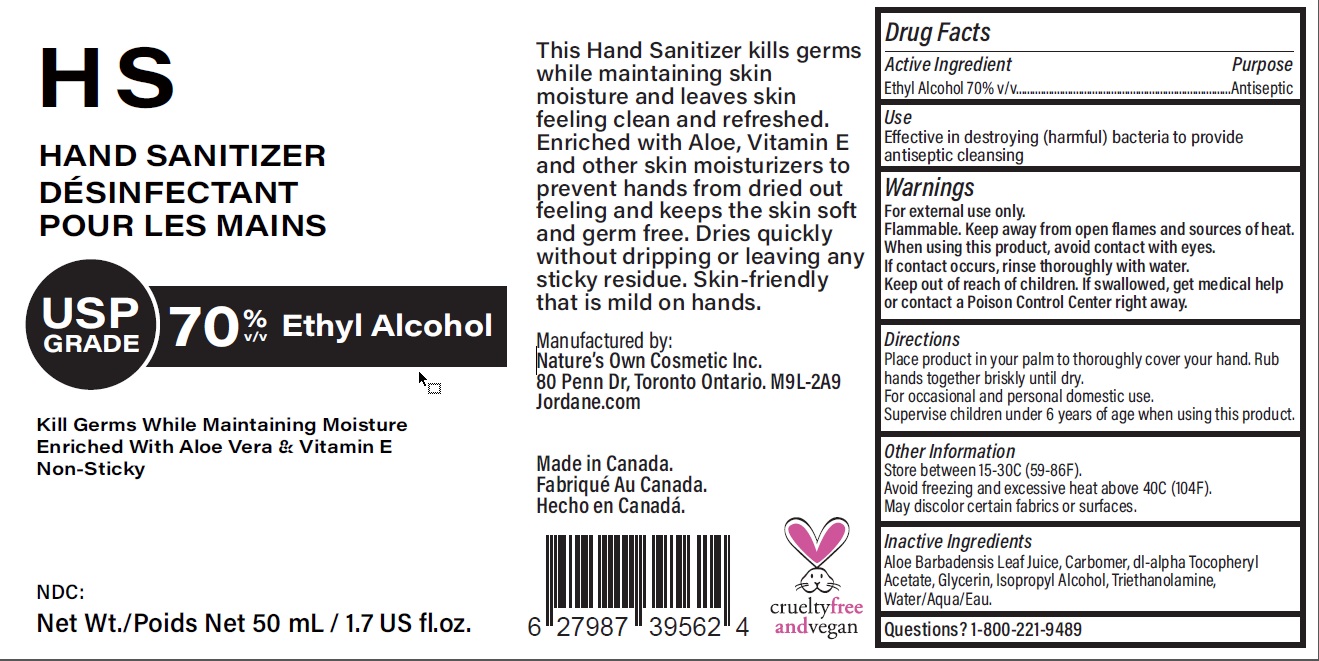 DRUG LABEL: HS Hand Sanitizer
NDC: 73756-003 | Form: GEL
Manufacturer: Nature’s Own Cosmetics Company Inc.
Category: otc | Type: HUMAN OTC DRUG LABEL
Date: 20201023

ACTIVE INGREDIENTS: ALCOHOL 70 mL/100 mL
INACTIVE INGREDIENTS: ALOE VERA LEAF; CARBOMER HOMOPOLYMER TYPE C (ALLYL PENTAERYTHRITOL CROSSLINKED); .ALPHA.-TOCOPHEROL ACETATE, DL-; GLYCERIN; ISOPROPYL ALCOHOL; TROLAMINE; WATER

Active Ingredient

Ethyl alcohol 70% v/v.

Purpose

Antiseptic

Use

Effective in destroying (harmful) bacteria to provide antiseptic cleansing.

Warnings

For external use only.
Flammable. Keep away from open flames and sources of heat.
When using this product, avoid contact with eyes. If contact occurs, rinse thoroughly with water.

Keep out of reach of children. If swallowed, get medical help or contact a Poison Control Center right away.

Directions

Place product in your palm to thoroughly cover your hand. Rub hands together briskly until dry.
For occasional and personal domestic use.
Supervise children under 6 years of age when using this product.

Other information

Store between 15-30C (59-86F).
Avoid freezing and excessive heat above 40C (104F).
May discolor certain fabrics or surfaces.

Inactive ingredients

Aloe Barbadensis Leaf Juice, Carbomer, dl-alpa Tocopheryl Acetate, Glycerin, lsopropyl Alcohol, Triethanolamine, Water/Aqua/Eau

Questions? 1-800-221-9489